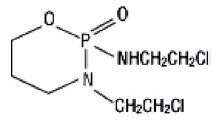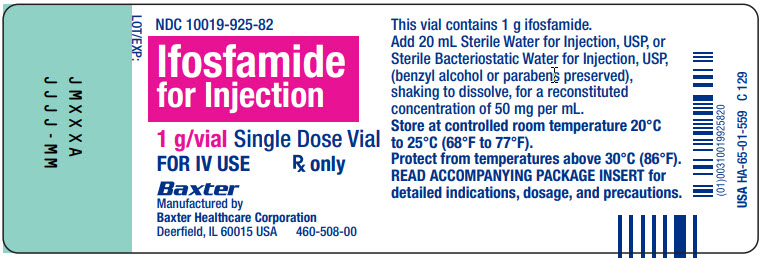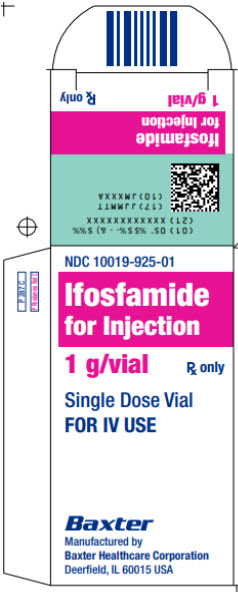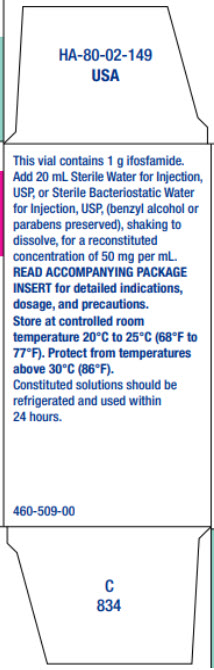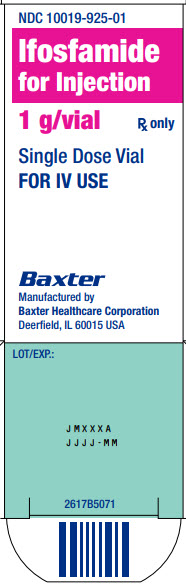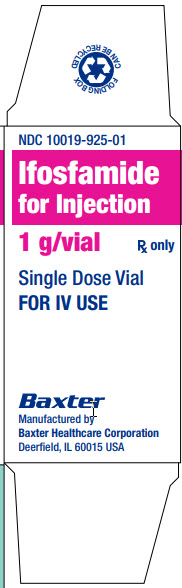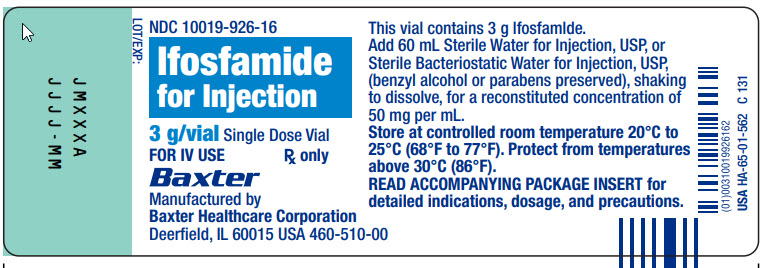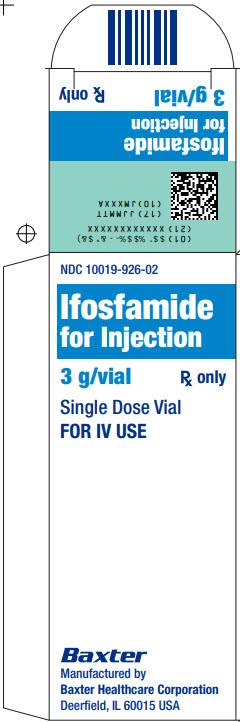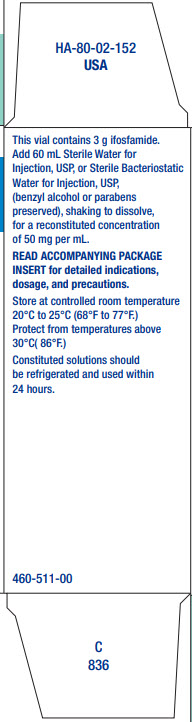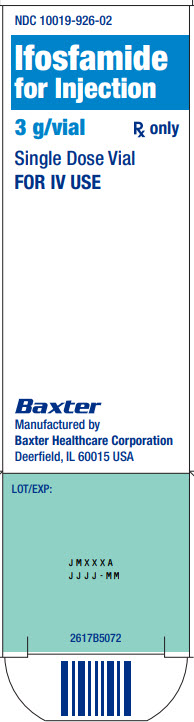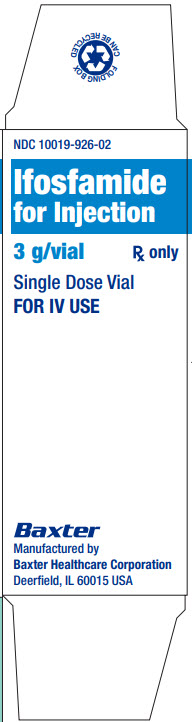 DRUG LABEL: IFOSFAMIDE
NDC: 10019-925 | Form: INJECTION, POWDER, FOR SOLUTION
Manufacturer: Baxter Healthcare Corporation
Category: prescription | Type: HUMAN PRESCRIPTION DRUG LABEL
Date: 20241202

ACTIVE INGREDIENTS: IFOSFAMIDE 1 g/20 mL

HIGHLIGHTS OF PRESCRIBING INFORMATION

These highlights do not include all the information needed to use Ifosfamide for Injection safely and effectively. See full prescribing information for Ifosfamide for Injection.
Ifosfamide for injection, intravenous use
Initial U.S. Approval: 1988

RECENT MAJOR CHANGES

Boxed Warning 12/2024

Dosage and Administration (2.1, 2.2, 2.3) 12/2024

Warnings and Precautions (5) 12/2024

WARNING: MYELOSUPPRESSION, ENCEPHALOPATHY, NEPHROTOXICITY and UROTOXICITY

See full prescribing information for complete boxed warning.

- Myelosuppression can be severe and lead to fatal infections (5.1)
- Encephalopathy can be severe and may result in death (5.2)
- Nephrotoxicity can be severe and result in renal failure. Hemorrhagic cystitis can be severe. (5.3)

1 INDICATIONS AND USAGE

Ifosfamide for Injection is an alkylating drug indicated for use in adults in combination with certain other approved antineoplastic agents for third-line chemotherapy of germ cell testicular cancer. (1)

2 DOSAGE AND ADMINISTRATION

- Administer Ifosfamide for Injection with extensive hydration consisting of at least 2 liters of oral or intravenous fluid per day to reduce the incidence or severity of bladder toxicity. (2.1, 5.3)
- Administer mesna with Ifosfamide for Injection to reduce the incidence or severity of hemorrhagic cystitis. (2.1, 5.3)
- Administer Ifosfamide for Injection as a slow intravenous infusion (at least 30 minutes) at a dose of 1.2 grams per m^2 per day for 5 consecutive days. Repeat every 3 weeks or after recovery from hematologic toxicity. (2.2)
- Individualize the dose and dosing schedule of Ifosfamide for Injection based on patient risk factors and adverse reactions. (2.2)
- See Full Prescribing Information for instructions on preparation and administration. (2.3)

3 DOSAGE FORMS AND STRENGTHS

- For injection: Single dose vials: 1 gram, 3 grams (3)

4 CONTRAINDICATIONS

- Known hypersensitivity to administration of ifosfamide. (4)
- Urinary outflow obstruction. (4)

5 WARNINGS AND PRECAUTIONS

- Myelosuppression: Monitor blood counts prior to treatment, during treatment, and as clinically indicated. (5.1)
- Encephalopathy: Monitor for signs and symptoms of CNS toxicity during and after Ifosfamide for Injection treatment. Dose interruption or permanent discontinuation may be required based on individual safety and tolerability. (5.2)
- Nephrotoxicity and Urotoxicity: Monitor signs and symptoms. Monitor serum and urine chemistries. (2.1, 5.3)
- Cardiotoxicity: Arrhythmias, other ECG changes, and cardiomyopathy can occur and result in death. Cardiotoxicity is dose dependent and the risk is increased in patients with preexisting cardiac, treatment with other cardiotoxic agents, radiation, and renal impairment. (5.4)
- Pulmonary toxicity: Interstitial pneumonitis, pulmonary fibrosis, and pulmonary toxicity with fatal outcomes can occur. Monitor for signs and symptoms of pulmonary toxicity and treat as clinically indicated. (5.5)
- Secondary malignancies can occur. (5.6)
- Veno-occlusive Liver Disease can occur. (5.7)
- Embryo-Fetal Toxicity: Can cause fetal harm. Advise of potential risk to a fetus and use of effective contraception. (5.8, 8.1, 8.3)
- Infertility: Can impair male and female reproductive function. (5.9)
- Anaphylactic/anaphylactoid reactions have been reported. (5.10)

6 ADVERSE REACTIONS

The most common (≥ 10%) adverse reactions were alopecia, nausea/vomiting, hematuria, leukopenia, anemia, CNS toxicity, infection. (6.1)

To report SUSPECTED ADVERSE REACTIONS, contact Baxter Healthcare at phone: 1 866 888 2472 or FDA at 1-800-FDA-1088 or www.fda.gov/medwatch.

7 DRUG INTERACTIONS

- CYP3A4 Inducers: Monitor for increased toxicity when used in combination with CYP3A4 inducers. (7.1)
- CYP3A4 Inhibitors: Use in combination with CYP3A4 inhibitors could decrease the effectiveness of ifosfamide. (7.2)

8 USE IN SPECIFIC POPULATIONS

- Lactation: Advise not to breastfeed. (8.2)
- Renal impairment: Closely monitor for adverse reactions and consider dosage modifications. (8.6)

FULL PRESCRIBING INFORMATION

WARNING: MYELOSUPPRESSION, ENCEPHALOPATHY, NEPHROTOXICITY and UROTOXICITY

- Myelosuppression can be severe and lead to fatal infections. Monitor blood counts prior to and at intervals after each treatment cycle [see Warnings and Precautions (5.1)].
- Encephalopathy can be severe and may result in death. Monitor for CNS toxicity and discontinue treatment for encephalopathy [see Warnings and Precautions (5.2)].
- Nephrotoxicity can be severe and result in renal failure. Hemorrhagic cystitis can be severe and can be reduced by the prophylactic use of mesna [see Warnings and Precautions (5.3)].

1 INDICATIONS AND USAGE

Ifosfamide for Injection is indicated for use in adults in combination with certain other approved antineoplastic agents for third-line chemotherapy of germ cell testicular cancer.

2 DOSAGE AND ADMINISTRATION

2.1 Important Administration Instructions

Administer Ifosfamide for Injection with extensive hydration consisting of at least 2 liters of oral or intravenous fluid per day to reduce the incidence or severity of bladder toxicity.

Administer Ifosfamide for Injection with mesna to reduce the incidence or severity of hemorrhagic cystitis [see Warnings and Precautions (5.3)].

2.2 Recommended Dosage

The recommended dosage of Ifosfamide for Injection is 1.2 grams per m2 per day administered as a slow intravenous infusion (lasting at least 30 minutes) for 5 consecutive days. Treatment is repeated every 3 weeks or after recovery from hematologic toxicity.

Individualize the dose and dosing schedule of Ifosfamide for Injection based on patient risk factors and adverse reactions.

2.3 Preparation and Administration

Ifosfamide for Injection is a hazardous drug. Follow applicable special handling and disposal procedures.1

Skin reactions associated with accidental exposure to Ifosfamide for Injection may occur. To minimize the risk of dermal exposure, always wear impervious gloves when handling vials and solutions containing Ifosfamide for Injection. If Ifosfamide for Injection solution contacts the skin or mucosa, immediately wash the skin thoroughly with soap and water or rinse the mucosa with copious amounts of water.

Prepare Ifosfamide for Injection for intravenous use by adding Sterile Water for Injection, USP or Bacteriostatic Water for Injection, USP (benzyl alcohol or parabens preserved) to the vial and shaking to dissolve. Before administration, the substance must be completely dissolved. Use the quantity of diluents shown in below to reconstitute the product:

Table 1: Ifosfamide for Injection Quantities for Dilution and Final Concentrations
Dosage Strength | Quantity of Diluent | Final Concentration
1 gram | 20 mL | 50 mg per mL
3 grams | 60 mL | 50 mg per mL

Solutions of ifosfamide may be diluted further to achieve concentrations of 0.6 to 20 mg/mL in the following fluids:

- 5% Dextrose Injection, USP
- 0.9% Sodium Chloride Injection, USP
- Lactated Ringer’s Injections, USP
- Sterile Water for Injection, USP

Because essentially identical stability results were obtained for Sterile Water admixtures as for the other admixtures (5% Dextrose Injection, 0.9% Sodium Chloride Injection, and Lactated Ringer’s Injection), the use of large volume parenteral glass bottles, VIAFLEX bags or PAB bags that contain intermediate concentrations or mixtures of excipients (e.g., 2.5% Dextrose Injection, 0.45% Sodium Chloride Injection, or 5% Dextrose and 0.9% Sodium Chloride Injection) is also acceptable.

Refrigerate constituted or constituted and further diluted solutions of Ifosfamide for Injection and use within 24 hours. Benzyl-alcohol-containing solutions can reduce the stability of ifosfamide.

Parenteral drug products should be inspected visually for particulate matter and discoloration prior to administration, whenever solution and container permit.

3 DOSAGE FORMS AND STRENGTHS

For injection: white, crystalline powder available in:

- 1 gram single-dose vial for reconstitution
- 3 gram single-dose vial for reconstitution

4 CONTRAINDICATIONS

Ifosfamide for Injection is contraindicated in patients with:

- Known hypersensitivity to administration of ifosfamide.
- Urinary outflow obstruction.

5 WARNINGS AND PRECAUTIONS

5.1 Myelosuppression

Ifosfamide for Injection can cause myelosuppression that results in severe or fatal infections including sepsis or septic shock. Ifosfamide‑induced myelosuppression includes leukopenia, neutropenia, thrombocytopenia (with bleeding events), and anemia. The nadir of the leukocyte count usually occurs during the second week after administration of Ifosfamide for Injection. The risk of myelosuppression is dose‑dependent and increased in patients with reduced renal function, bone marrow metastases, prior radiation, and concomitant or prior therapy with other cytotoxic agents.

Monitor complete blood counts, including leukocytes, neutrophils, platelets, and hemoglobin prior to each administration of Ifosfamide for Injection, at appropriate intervals during treatment, and as clinically indicated.

Myelosuppression may require dosage delays. Avoid administration of Ifosfamide for Injection to patients with a WBC count below 2000/µL, a platelet count below 50,000/µL, or when signs or symptoms of active infection or severe immunosuppression are present.

5.2 Encephalopathy

Ifosfamide for Injection can cause encephalopathy which may be fatal. Signs and symptoms may include confusion, somnolence, coma, hallucination, blurred vision, psychotic behavior, extrapyramidal symptoms, urinary incontinence, and seizures.

Risk factors include high ifosfamide dosage, hypoalbuminemia, impaired renal function, poor performance status, bulky abdominal-pelvic disease, nephrotoxic treatments including cisplatin, CNS active drugs, or alcohol use.

Signs and symptoms may occur or recur within hours to days after administration of Ifosfamide for Injection. Continue supportive care until complete resolution of CNS signs and symptoms.

Monitor for signs and symptoms of encephalopathy during and after Ifosfamide for Injection treatment. Dose interruption or permanent discontinuation may be required based on individual safety and tolerability. Consider methylene blue for treatment of encephalopathy.

5.3 Nephrotoxicity and Urotoxicity

Ifosfamide for Injection can cause severe or fatal nephrotoxicity and urotoxicity including glomerular or tubular dysfunction, tubular necrosis, renal parenchymal necrosis, acute renal failure, chronic renal failure, and hemorrhagic cystitis (requiring blood transfusion).

Tubular damage may occur up to years after cessation of Ifosfamide for Injection treatment. The risk of nephrotoxicity is increased in patients with renal impairment or reduced nephron reserve. Hemorrhagic cystitis is dose‑dependent and the risk is increased with past or concomitant radiation of the bladder or busulfan treatment.

Evaluate glomerular and tubular kidney function before treatment with Ifosfamide for Injection, during Ifosfamide for Injection treatment, and as clinically indicated. Monitor serum and urine chemistries (including phosphorus and potassium) and urinary sediment for the presence of erythrocytes or other signs of nephrotoxicity. Signs and symptoms may include a decrease in glomerular filtration rate, increased serum creatinine, proteinuria, enzymuria, cylindruria, aminoaciduria, phosphaturia, glycosuria, osteomalacia, tubular acidosis, Fanconi syndrome, and syndrome of inappropriate antidiuretic hormone secretion (SIADH).

Before starting treatment, exclude or correct any urinary tract obstructions [see Contraindications (4)]. During or immediately after administration, provide oral or intravenous fluid to force dieresis to reduce the risk of urinary tract toxicity. Administer mesna with Ifosfamide for Injection to reduce the incidence and severity of urotoxicity [see Dosage and Administration (2.1)].

Obtain a urinalysis prior to each dose of Ifosfamide for Injection. Avoid administration of Ifosfamide for Injection in patients with active urinary tract infections. If microscopic hematuria (greater than 10 RBCs per high power field) is present, then withhold administration of Ifosfamide for Injection until complete resolution. Further administration of Ifosfamide for Injection should be given with vigorous oral or parenteral hydration. Dosage interruption or permanent discontinuation may be required based on individual safety and tolerability.

5.4 Cardiotoxicity

Ifosfamide for Injection can cause severe or fatal cardiotoxicity including any of the following:

- Supraventricular or ventricular arrhythmias, including atrial/supraventricular tachycardia, atrial fibrillation, pulseless ventricular tachycardia
- Decreased QRS voltage and ST-segment or T-wave changes
- Toxic cardiomyopathy leading to heart failure with congestion and hypotension
- Pericardial effusion, fibrinous pericarditis, and epicardial fibrosis

Cardiotoxic effects are dose‑dependent and the risk is increased in patients with cardiac disease, prior or concomitant treatment with other cardiotoxic agents, radiation of the cardiac region, and renal impairment.

5.5 Pulmonary Toxicity

Ifosfamide for Injection can cause severe or fatal pulmonary toxicities including interstitial pneumonitis, pulmonary fibrosis, and respiratory failure. Monitor for signs and symptoms of pulmonary toxicity and treat as clinically indicated.

5.6 Secondary Malignancies

The incidence of secondary malignancies is increased in patients treated with Ifosfamide for Injection-containing regimens. Cases of myelodysplastic syndrome, acute leukemias, lymphomas, thyroid cancers, and sarcomas have occurred and may develop several years after chemotherapy has been discontinued.

5.7 Veno-occlusive Liver Disease

Veno-occlusive liver disease has been reported with chemotherapy that included ifosfamide.

5.8 Embryo-Fetal Toxicity

Based on mechanism of action and human and animal data, Ifosfamide for Injection can cause fetal harm when administered to a pregnant woman [see Use in Specific Populations (8.1), Clinical Pharmacology (12.1) and Nonclinical Toxicology (13.1)]. Fetal growth retardation and neonatal anemia have been reported following exposure to ifosfamide‑containing chemotherapy regimens during pregnancy. Ifosfamide is genotoxic and mutagenic in male and female germ cells. Embryotoxic and teratogenic effects have been observed in mice, rats and rabbits at doses 0.05 to 0.075 times the human dose.

Advise pregnant women and females of reproductive potential of the potential risk to the fetus [see Use in Specific Populations (8.1)]. Verify the pregnancy status of females of reproductive potential prior to initiation of Ifosfamide for Injection. Advise females of reproductive potential to use effective contraception during treatment with Ifosfamide for Injection and for up to 12 months after completion of therapy.

Advise male patients with female partners of reproductive potential to use effective contraception during treatment with Ifosfamide for Injection and for 6 months after completion of therapy [see Use in Specific Populations (8.1, 8.3)].

5.9 Infertility

Male and female reproductive function and fertility may be impaired in patients treated with Ifosfamide for Injection. Ifosfamide interferes with oogenesis and spermatogenesis. Amenorrhea, azoospermia; and sterility in both sexes have been reported. Development of sterility appears to depend on the dose of ifosfamide, duration of therapy, and state of gonadal function at the time of treatment. Sterility may be irreversible in some patients. Advise patients on the potential risks for infertility [see Use in Specific Populations (8.3 and 8.4)].

5.10 Anaphylactic/Anaphylactoid Reactions and Cross-sensitivity

Anaphylactic/anaphylactoid reactions have been reported in association with ifosfamide. Cross-sensitivity between oxazaphosphorine cytotoxic agents has been reported.

5.11 Impairment of Wound Healing

Ifosfamide may interfere with normal wound healing.

6 ADVERSE REACTIONS

6.1 Clinical Trials Experience

Because clinical trials are conducted from widely varying conditions, adverse reaction rates observed in the clinical trials of a drug cannot be directly compared to rates in the clinical trials of another drug and may not reflect the rates observed in clinical practice.

The adverse reactions in Table 2 below are based on 30 publications describing clinical experience with fractionated administration of ifosfamide as a single agent with a total dose of 4 to 12 g/m^2 per course.

Table 2: Adverse Reactions in Patients Treated with Single Agent Ifosfamide for Injection
Adverse Reaction | Single Agent Ifosfamide for Injection % (number of patients)
Skin and Subcutaneous Tissue Disorders
Alopecia | 90%; (540/603)
Dermatitis | 0.08%; (1/1317)
Papular rash | 0.08%; (1/1317)
Gastrointestinal Disorders
Nausea/Vomiting | 47%; (443/964)
Diarrhea | 0.7%; (9/1317)
Stomatitis | 0.3%; (4/1317)
Renal and Urinary Disorders
Hemorrhagic cystitis [Includes dysuria and pollakiuria]
Hematuria
- without mesna | 44%; (282/640)
- with mesna | 21%; (33/155)
Macrohematuria
- without mesna | 11%; (66/594)
- with mesna | 5%; (5/97)
Renal dysfunction [Includes acute renal failure, irreversible renal failure (fatal outcomes) serum creatinine increased, BUN increased, creatinine clearance decreased, metabolic acidosis, anuria, oliguria, glycosuria, hyponatremia, uremia, creatinine clearance increased] | --
Renal structural damage [Includes acute tubular necrosis, renal parenchymal damage, enzymuria, cylindruria, proteinuria] | --
Blood and Lymphatic System Disorders
Leukopenia [Includes neutropenia, granulocytopenia, lymphopenia, and pancytopenia] (any) | --
Leukopenia; <1 x 10^3/µL | 44%; (267/614)
Anemia [Includes anemia and decrease in hemoglobin/hematocrit] | 38%; (202/533)
- with mesna | 21.3%; (33/155)
Thrombocytopenia [Includes severe or fatal bleeding] (any) | --
Thrombocytopenia, 50 x 10^3/µL | 4.8%; (35/729)
Nervous System Disorders
Central nervous system toxicity [Includes coma and death] [Includes abnormal behavior, affect lability aggression, agitation, anxiety, aphasia, asthenia, ataxia, cerebellar syndrome, cerebral function deficiency, cognitive disorder, coma, confusional state, convulsions, cranial nerve dysfunction, depressed state of consciousness, depression, disorientation, dizziness, electroencephalogram abnormal, encephalopathy, flat affect, hallucinations, headache, ideation, lethargy, memory impairment, mood change, motor dysfunction, muscle spasms, myoclonus, progressive loss of brainstem reflexes, psychotic reaction, restlessness, somnolence, tremor, urinary incontinence] | 15%; (154/1001)
Peripheral neuropathy | 0.4%; (5/1317)
Infections and Infestations
Infection | 10%; (112/1128)
General Disorders and Administration Site Conditions
Phlebitis [Includes phlebitis and irritation of the venous walls] | 2.8%; (37/1317)
Neutropenic fever [Includes granulocytopenic fever] | 1%; (13/1317)
Fatigue | 0.3%; (4/1317)
Malaise | Unable to calculate
Hepatobiliary Disorders
Hepatotoxicity [Includes increased serum alanine aminotransferase (ALT), serum aspartate aminotransferase (AST), alkaline phosphatase, gamma-glutamyltransferase (GGT) and lactate dehydrogenase (LDH)] | 1.8%; (22/1190)
Metabolism and Nutrition Disorders
Anorexia | 1.1%; (15/1317)
Cardiac Disorders
Cardiotoxicity [Includes severe or fatal congestive heart failure, tachycardia, pulmonary edema] | 0.5%; (7/1317)
Vascular Disorders
Hypotension [Includes shock and death] | 0.3%; (4/1317)

6.2 Postmarketing Experience

The following adverse reactions have been identified during post-approval use of Ifosfamide for Injection. Because these reactions are reported voluntarily from a population of uncertain size, it is not always possible to reliably estimate their frequency or establish a causal relationship to drug exposure.

Blood and Lymphatic Disorders: agranulocytosis, febrile bone marrow aplasia, bone marrow failure, disseminated intravascular coagulation, hemolytic anemia, hemolytic febrile uremic syndrome, methemoglobinemia, neonatal anemia

Cardiac Disorders: cardiac arrest*, cardiac failure*, arrhythmia*, cardiomyopathy*, cardiotoxicity, cardiac shock, ejection fraction decreased*, myocardial infarction*, myocarditis*, ventricular fibrillation*, ventricular tachycardia*, angina pectoris, atrial fibrillation, atrial flutter, bradycardia, bundle branch block left, bundle branch block right, congestive cardiomyopathy, electrocardiogram ST – segment abnormal, electrocardiogram QRD complex abnormal, electrocardiogram T-wave inversion, myocardial depression, myocardial hemorrhage, left ventricular failure, premature atrial contractions, palpitations pericardial effusion, pericarditis, supraventricular extrasystoles, ventricular extrasystoles

Congenital Disorders: fetal growth retardation

Ear Disorders: deafness, hypoacusis, tinnitus, vertigo

Endocrine Disorder: SIADH

Eye Disorders: conjunctivitis, eye irritation, vision blurred, visual impairment

Gastrointestinal Disorders: abdominal pain, cecitis, colitis, constipation, enterocolitis, ileus, gastrointestinal hemorrhage, mucosal ulceration, pancreatitis, salivary hypersecretion

General Disorders and Administrative Site Conditions: multi‑organ failure*, chest pain, chills, injection/infusion site reactions (including erythema, inflammation, pain, pruritus, swelling, tenderness), edema, general physical deterioration, mucosal inflammation, pain, pyrexia

Hepatobiliary Disorders: hepatic failure*, hepatitis fulminant*, cholestasis, cytolytic hepatitis, portal vein thrombosis, veno‑occlusive liver disease

Immune System Disorders: anaphylactic reaction, angioedema, hypersensitivity reaction, immunosuppression, urticaria

Infections:

The following manifestations have been associated with myelosuppression and immunosuppression caused by ifosfamide: increased risk for and severity of infections†, pneumonias†, sepsis and septic shock (including fatal outcomes), as well as reactivation of latent infections, including viral hepatitis†, Pneumocystis jiroveci†, herpes zoster, Strongyloides, progressive multifocal leukoencephalopathy†, and other viral and fungal infections.

† Severe immunosuppression has led to serious, sometimes fatal, infections

Metabolic and Nutrition Disorders: hypocalcemia, hypokalemia, hypophosphatemia, hyperglycemia, metabolic acidosis, polydipsia, tumor lysis syndrome

Musculoskeletal and Connective Tissue Disorders: arthralgia, growth retardation, myalgia, muscle twitching, osteomalacia, pain in extremity, rhabdomyolysis, rickets

Neoplasms: secondary malignancies*, acute lymphocytic leukemia, acute myeloid leukemia, acute promyelocytic leukemia, myelodysplastic syndrome, Non‑Hodgkin’s lymphoma, renal cell carcinoma, sarcomas, thyroid cancer

Nervous System Disorders: seizure*, asterixis, dysarthria, dysesthesia, extrapyramidal disorder, fecal incontinence, gait disturbance hypothesia, leukoencephalopathy, movement disorder, neuralgia, paresthesia, polyneuropathy, reversible posterior leukoencephalopathy syndrome. Ifosfamide has been reintroduced after neurotoxicity. While some patients did not experience neurotoxicity, others had recurrent, including fatal, events.

Psychiatric Disorders: amnesia, bradyphrenia, catatonia, delirium, delusion, echolalia, logorrhea, mania mental status change, mutism, paranoia, panic attack, perseveration

Renal and Urinary Disorders: aminoaciduria, diabetes insipidus, enuresis, Fanconi syndrome, feeling of residual urine, nephrogenic phosphaturia, polyuria, tubulointerstitial nephritis

Reproductive System and Breast Disorders: amenorrhea, azoospermia, decreased blood estrogen, impairment of spermatogenesis, increased blood gonadotrophin, infertility, oligospermia, ovarian failure, ovulation disorder, premature menopause

Respiratory, Thoracic, and Mediastinal Disorders: acute respiratory distress syndrome*, pulmonary fibrosis*, pneumonitis*/interstitial lung disease*, pulmonary edema*, pulmonary hypertension*, respiratory failure*, alveolitis allergic, bronchospasm, cough, dyspnea, hypoxia, pleural effusion

Skin and Subcutaneous Disorders: erythema, facial swelling, hyperhidrosis, macular rash, nail disorder, palmar‑plantar erythrodysesthesia syndrome, petechiae, pruritus, radiation recall dermatitis, rash, skin hyperpigmentation, skin necrosis, Stevens‑Johnson syndrome, toxic epidermal necrolysis

Vascular Disorders: capillary leak syndrome, deep vein thrombosis, flushing, hypertension, pulmonary embolism, vasculitis

* Includes fatal outcomes

7 DRUG INTERACTIONS

7.1 Inducers of CYP3A4

CYP3A4 inducers may increase the metabolism of ifosfamide to its active alkylating metabolites. CYP3A4 inducers may increase the formation of the neurotoxic/nephrotoxic ifosfamide metabolite, chloroacetaldehyde. Closely monitor patients taking ifosfamide with CYP3A4 inducers for toxicities and consider dose adjustment.

7.2 Inhibitors of CYP3A4

CYP3A4 inhibitors may decrease the metabolism of ifosfamide to its active alkylating metabolites, perhaps decreasing the effectiveness of ifosfamide treatment.

8 USE IN SPECIFIC POPULATIONS

8.1 Pregnancy

Risk Summary

Based on mechanism of action [see Clinical Pharmacology (12.1)], and human and animal data (see Data), Ifosfamide for Injection can cause fetal harm when administered to a pregnant woman. Fetal growth retardation and neonatal anemia have been reported following exposure to ifosfamide‑containing chemotherapy regimens during pregnancy.

In the U.S. general population, the estimated background risk of major birth defects and miscarriage in clinically recognized pregnancies is 2 to 4% and 15 to 20%, respectively.

Data

Animal Data

Animal studies indicate that ifosfamide is capable of causing gene mutations and chromosomal damage in vivo. In pregnant mice, resorptions increased and anomalies were present at day 19 after a 30 mg/m^2 dose of ifosfamide was administered on day 11 of gestation. Embryo-lethal effects were observed in rats following the administration of 54 mg/m^2 doses of ifosfamide from the 6th through the 15th day of gestation and embryotoxic effects were apparent after dams received 18 mg/m^2 doses over the same dosing period. Ifosfamide is embryotoxic to rabbits receiving 88 mg/m^2/day doses from the 6th through the 18th day after mating. The number of anomalies was also significantly increased over the control group.

8.2 Lactation

Risk Summary

Ifosfamide is excreted in breast milk. Because of the potential for serious adverse events, and the tumorigenicity shown for ifosfamide in animal studies, advise women not to breastfeed during treatment with Ifosfamide for Injection and for one week after the last dose.

8.3 Females and Males of Reproductive Potential

Ifosfamide for Injection can cause fetal harm when administered to a pregnant woman [see Use in Specific Populations (8.1)].

Pregnancy Testing

Verify pregnancy status in females of reproductive potential prior to initiating Ifosfamide for Injection [see Use in Specific Populations (8.1)].

Contraception

Females

Advise female patients of reproductive potential to use effective contraception during treatment with Ifosfamide for Injection and for 12 months after the last dose.

Males

Advise males with female sexual partners of reproductive potential to use effective contraception during treatment with Ifosfamide for Injection and for 6 months after the last dose [see Nonclinical Toxicology (13.1)].

Infertility

Females

Amenorrhea has been reported in patients treated with ifosfamide. The risk of permanent chemotherapy induced amenorrhea increases with age.

Males

Men treated with ifosfamide may develop oligospermia or azoospermia. Azoospermia may be reversible in some patients, though the reversibility may not occur for several years after cessation of therapy. Sexual function and libido are generally unimpaired in these patients. Some degree of testicular atrophy may occur. Patients treated with ifosfamide have subsequently fathered children.

Females and Males

Based on animal studies, Ifosfamide for Injection may impair fertility in females and males of reproductive potential. The reversibility of these effects is unknown [see Nonclinical Toxicology (13.1)].

8.4 Pediatric Use

Safety and effectiveness have not been established in pediatric patients.

Renal rickets and growth retardation in pediatric patients treated with ifosfamide have been reported.

Ifosfamide for Injection may cause temporary or permanent infertility in prepubertal girls or in females of child-bearing potential and may have an increased risk of developing premature menopause.

Ifosfamide for Injection may cause abnormal secondary sexual characteristic development in prepubertal males. Sterility, azoospermia, and testicular atrophy have been reported in male patients. Azoospermia may be reversible in some patients, but may not occur for several years after cessation of Ifosfamide for Injection therapy.

8.5 Geriatric Use

Clinical studies of Ifosfamide for Injection did not include sufficient numbers of patients aged 65 and over to determine whether they respond differently from younger subjects.

A study of patients 40 to 71 years of age indicated that elimination half-life appears to increase with advancing age [see Pharmacokinetics (12.3)]. This apparent increase in half-life appeared to be related to increases in volume of distribution of ifosfamide with age. No significant changes in total plasma clearance or renal or non-renal clearance with age were reported.

Ifosfamide and its metabolites are known to be substantially excreted by the kidney, and the risk of toxic reactions to this drug may be greater in patients with impaired renal function. Because elderly patients are more likely to have decreased renal function, closely monitor for adverse reactions and monitor renal function as clinically indicated.

8.6 Use in Patients with Renal Impairment

Ifosfamide and its metabolites are known to be excreted by the kidneys and may accumulate in plasma with decreased renal function. Closely monitor patients with renal impairment for adverse reactions and consider dosage modifications. Ifosfamide and its metabolites are dialyzable.

8.7 Use in Patients with Hepatic Impairment

Ifosfamide is extensively metabolized in the liver and forms both efficacious and toxic metabolites. Closely monitor patients with impaired hepatic function for adverse reactions during treatment with Ifosfamide for Injection.

10 OVERDOSAGE

No specific antidote for Ifosfamide for Injection is known.

Patients who receive an overdose should be closely monitored for the development of toxicities. Serious consequences of overdosage include manifestations of dose-dependent toxicities such as CNS toxicity, nephrotoxicity, myelosuppression, and mucositis [see Warnings and Precautions (5)].

Management of overdosage would include general supportive measures to sustain the patient through any period of toxicity that might occur, including appropriate state-of-the-art treatment for any concurrent infection, myelosuppression, or other toxicity. Ifosfamide as well as ifosfamide metabolites are dialyzable.

Cystitis prophylaxis with mesna may be helpful in preventing or limiting urotoxic effects with overdose.

11 DESCRIPTION

Ifosfamide for Injection (ifosfamide for injection, USP) single-dose vials for constitution and administration by intravenous infusion each contain 1 gram or 3 grams of sterile ifosfamide.

Ifosfamide is a alkylating drug chemically related to the nitrogen mustards and a synthetic analog of cyclophosphamide. Ifosfamide is 3-(2-chloroethyl)-2-[(2-chloroethyl)amino]tetrahydro-2H-1,3,2-oxazaphosphorine 2-oxide. The molecular formula is C7H15Cl2N2O2P and its molecular weight is 261.1. Ifosfamide is a white crystalline powder soluble in water. There are no excipients in the formulation. Each vial contains 1 gram or 3 grams of sterile ifosfamide alone.

Its structural formula is:

12 CLINICAL PHARMACOLOGY

12.1 Mechanism of Action

Ifosfamide is a prodrug that requires metabolic activation by hepatic cytochrome P450 isoenzymes to exert its cytotoxic activity. Activation occurs by hydroxylation at the ring carbon atom forming the unstable intermediate 4‑hydroxyifosfamide and its ring-opened aldo tautomer, which decomposes to yield the cytotoxic and urotoxic compound acrolein and an alkylating isophosphoramide mustard isophosphoramide mustard.

The exact mechanism of action of ifosfamide has not been determined, but its cytotoxic action is primarily through DNA crosslinks caused by alkylation by the isophosphoramide mustard at guanine N-7 positions. The formation of inter- and intra-strand cross-links in the DNA results in cell death.

12.3 Pharmacokinetics

Ifosfamide exhibits dose-dependent pharmacokinetics in humans. At single doses of 3.8 to 5.0 g/m^2, the plasma concentrations decay biphasically and the mean terminal elimination half-life is about 15 hours. At doses of 1.6 to 2.4 g/m^2/day, the plasma decay is monoexponential and the terminal elimination half-life is about 7 hours.

Ifosfamide exhibits time-dependent pharmacokinetics in humans. Following intravenous administration of 1.5 g/m^2 over 0.5 hour once daily for 5 days to 15 patients with neoplastic disease, a decrease in the median elimination half-life from 7.2 hour on Day 1 to 4.6 hours on Day 5 occurred with a concomitant increase in the median clearance from 66 mL/min on Day 1 to 115 mL/min on Day 5. There was no significant change in the volume of distribution on Day 5 compared with Day 1.

Distribution

Ifosfamide volume of distribution (Vd) approximates the total body water volume, suggesting that distribution takes place with minimal tissue binding. Following intravenous administration of 1.5 g/m^2 over 0.5 hour once daily for 5 days to 15 patients with neoplastic disease, the median Vd of ifosfamide was 0.64 L/kg on Day 1 and 0.72 L/kg on Day 5. Ifosfamide shows little plasma protein binding. Ifosfamide and its active metabolites are extensively bound by red blood cells. Ifosfamide is not a substrate for P-glycoprotein.

Metabolism

Ifosfamide is extensively metabolized in humans through two metabolic pathways: ring oxidation (“activation”) to form the active metabolite, 4-hydroxy-ifosfamide and side-chain oxidation to form the inactive metabolites, 3-dechloro-ethylifosfamide or 2-dechloroethylifosfamide with liberation of the toxic metabolite, chloroacetaldehyde. Small quantities (nmol/mL) of ifosfamide mustard and 4‑hydroxyifosfamide are detectable in human plasma. Metabolism of ifosfamide is required for the generation of the biologically active species and while metabolism is extensive, it is also quite variable among patients.

Excretion

After administration of doses of 5 g/m^2 of ^14C-labeled ifosfamide, from 70% to 86% of the dosed radioactivity was recovered in urine as metabolites, with about 61% of the dose excreted as parent compound. At doses of 1.6 to 2.4 g/m^2 only 12% to 18% of the dose was excreted in the urine as unchanged drug within 72 hours. Two different dechloroethylated derivatives of ifosfamide, 4-carboxyifosfamide, thiodiacetic acid and cysteine conjugates of chloroacetic acid have been identified as the major urinary metabolites of ifosfamide in humans and only small amounts of 4‑hydroxyifosfamide and acrolein are present.

Specific Populations

Pediatric Patients

Population PK analysis was performed on plasma data from 32 pediatric patients various malignant diseases aged between 1 and 18 years. Patients received a total of 45 courses of ifosfamide at doses of 1.2, 2.0 and 3.0 g/m^2 given intravenously over 1 or 3 hours on 1, 2, or 3 days. The mean±standard error population estimates for the initial clearance and volume of distribution of ifosfamide were 2.4±0.33 L/h/m^2 and 21±1.6 L/m^2 with an interindividual variability of 43% and 32%, respectively.

Effect of Age

A study of 20 patients between 40 to 71 years of age receiving 1.5 g/m^2 of ifosfamide daily for 3 or 5 days indicated that elimination half‑life appears to increase with age. The elimination half‑life increase appeared to be related to the increase in ifosfamide volume of distribution with age. No significant changes in total plasma clearance or renal clearance with age were reported.

13 NONCLINICAL TOXICOLOGY

13.1 Carcinogenesis, Mutagenesis, Impairment of Fertility

Ifosfamide has been shown to be carcinogenic in rats when administered by intraperitoneal injection at 6 mg/kg (37 mg/m^2, or about 3% of the daily human dose on a mg/m^2 basis) 3 times a week for 52 weeks. Female rats had a significantly higher incidence of uterine leiomyosarcomas and mammary fibroadenomas than vehicle controls.

The mutagenic potential of ifosfamide has been documented in bacterial systems in vitro and mammalian cells in vivo. In vivo, ifosfamide has induced mutagenic effects in mice and Drosophila melanogaster germ cells, and has induced a significant increase in dominant lethal mutations in male mice as well as recessive sex-linked lethal mutations in Drosophila.

Ifosfamide was administered to male and female beagle dogs at doses of 1.00 or 4.64 mg/kg/day (20 or 93 mg/m^2) orally 6 days a week for 26 weeks. Male dogs at 4.64 mg/kg (about 7.7% of the daily clinical dose on a mg/m^2 basis) had testicular atrophy with degeneration of the seminiferous tubular epithelium. In a second study, male and female rats were given 0, 25, 50, or 100 mg/kg (0, 150, 300, or 600 mg/m^2) ifosfamide intraperitoneally once every 3 weeks for 6 months. Decreased spermatogenesis was observed in most male rats given 100 mg/kg (about half the daily clinical dose on a mg/m^2 basis).

14 CLINICAL STUDIES

Patients with refractory testicular cancer (n=59) received a combination of ifosfamide, cisplatin, and either etoposide (VePesid) or vinblastine (VIP) as third-line therapy or later. The selection of etoposide or vinblastine (“V” in the VIP regimen) was guided by the therapeutic effect achieved with prior regimens. The contribution of ifosfamide to the VIP combination was determined in patients treated with cisplatin-etoposide prior to ifosfamide-cisplatin-etoposide or those who received cisplatin-vinblastine prior to ifosfamide-cisplatin-vinblastine.

A total of 59 patients received a third-line salvage regimen which consisted of ifosfamide 1.2 g/m^2/day intravenously on days 1 to 5, cisplatin 20 mg/m^2/day intravenously on days 1 to 5, and either etoposide 75 mg/m^2/day intravenously on days 1 to 5 or vinblastine 0.22 mg/kg intravenously on day 1. Efficacy results with the VIP regimen were compared to data pooled from six single agent phase II trials conducted between August 1980 and October 1985 including a total of 90 patients of whom 65 were eligible as controls of this study. Twenty-three patients in the VIP regimen became free of disease with VIP alone or VIP plus surgery, whereas a single patient in the historical control group achieved complete response. The median survival time exceeded two years in the VIP group versus less than one year in the control group. Performance status ≥ 80, embryonal carcinoma and minimal disease were favorable prognostic factors for survival. In all prognostic categories, the difference between VIP and historical controls remained highly significant.

Table 3: Efficacy Results
 | Number. (%) of Patients
 | VIP | Control | p-value
Total Patients | 59 (100) | 65 (100)
Disease-free | 23 (39) | 1 (2) | < 0.001
Chemotherapy alone | 15 (25) | 1 (2) | < 0.001
Chemotherapy plus surgery | 8 (14) | 0
Overall Response | 32 (54) | 2 (3) | < 0.001
Time to progression (weeks)
Median | 19 | 4 | < 0.001 [Gehan-Breslow and Mantel-Cox tests]
Range | 1 – 205+ | 1 – 29
Disease-free interval (weeks)
Median | 114 | 29
Range | 13 – 205+ | --
Survival (weeks)
Median | 53 | 10 | < 0.001
Range | 1 – 205+ | 1 – 123+

In a study, 50 fully evaluable patients with germ cell testicular cancer were treated with Ifosfamide for Injection in combination with cisplatin and either vinblastine or etoposide after failing (47 of 50 patients) at least two prior chemotherapy regimens consisting of cisplatin/vinblastine/bleomycin, (PVB), cisplatin/vinblastine/actinomycin D/bleomycin/cyclophosphamide, (VAB6), or the combination of cisplatin and etoposide. Patients were selected for remaining cisplatin sensitivity because they had previously responded to a cisplatin containing regimen and had not progressed while on the cisplatin containing regimen or within 3 weeks of stopping it. Patients served as their own control based on the premise that long term complete responses could not be achieved by retreatment with a regimen to which they had previously responded and subsequently relapsed.

Ten of 50 fully evaluable patients were still alive 2 to 5 years after treatment. Four of the 10 long term survivors were rendered free of cancer by surgical resection after treatment with the ifosfamide regimen; median survival for the entire group of 50 fully evaluable patients was 53 weeks.

15 REFERENCES

1. OSHA Hazardous Drugs. OSHA. http://www.osha.gov/SLTC/hazardousdrugs/index.html

16 HOW SUPPLIED/STORAGE AND HANDLING

Ifosfamide for injection is available in single-dose vials as follows:

NDC 10019-925-01 1-gram Single-Dose Vial

NDC 10019-926-02 3-gram Single-Dose Vial

Store at controlled room temperature 20°C to 25°C (68°F to 77°F).

Protect from temperatures above 30°C (86°F).

17 PATIENT COUNSELING INFORMATION

Myelosuppression

- Advise patients that treatment with Ifosfamide for Injection may cause myelosuppression which can be severe and lead to infections and fatal outcomes.
- Inform patients of the risks associated with the use of Ifosfamide for Injection and plan for regular blood monitoring during therapy [see Boxed Warning, Warnings and Precautions (5.1)].
- Inform patients to report fever or other symptoms of an infection [see Boxed Warning, Warnings and Precautions (5.1), Adverse Reactions (6.2)].
- Advise patients on the risks of bleeding and anemia [see Warnings and Precautions (5.1, 5.8), Adverse Reactions (6.2)], Use in Specific Populations (8.1)].

Encephalopathy

- Advise patients on the risk of encephalopathy and other neurotoxic effects with fatal outcome [see Boxed Warning, Warnings and Precautions (5.2)].
- Inform patients that Ifosfamide for Injection may impair the ability to operate an automobile or other heavy machinery [see Boxed Warning, Warnings and Precautions (5.2)].
Nephrotoxicity and Urotoxicity
- Advise patients on the risk of bladder and kidney toxicity.
- Advise patients of the need to increase fluid intake and frequent voiding to prevent accumulation in the bladder [see Warnings and Precautions (5.3)].

Cardiotoxicity

- Advise patients on the risk of cardiotoxicity and fatal outcome.
- Advise patients to report preexisting cardiac disease and manifestations of cardiotoxicity [see Warnings and Precautions (5.4), Adverse Reactions (6.2)].

Pulmonary Toxicity

- Advise patients on the risk of pulmonary toxicity leading to respiratory failure with fatal outcome.
- Inform patients to report signs and symptoms of pulmonary toxicity [see Warnings and Precautions (5.5)].

Secondary Malignancies

- Advise patients on the risk of secondary malignancies due to therapy [see Warnings and Precautions (5.6)].

Veno-occlusive Liver Disease

- Advise patients on the risk of veno-occlusive liver disease [see Warnings and Precautions (5.7)].

Embryo-Fetal Toxicity

- Advise pregnant women and females of reproductive potential of the potential risk to a fetus. Advise females to inform their healthcare provider of a known or suspected pregnancy [see Warnings and Precautions (5.8) and Use in Specific Populations (8.1)].
- Advise females of reproductive potential to use effective contraception during treatment with Ifosfamide for Injection and for 12 months after the last dose [see Use in Specific Populations (8.3)].
- Advise male patients with female partners of reproductive potential to use effective contraception during treatment with Ifosfamide for Injection and for 6 months after the last dose [see Use in Specific Populations (8.3)].

Lactation

- Advise women not to breastfeed during treatment with Ifosfamide for Injection and for 1 week after the last dose [see Use in Specific Populations (8.2)].
  Infertility
- Advise females and males of reproductive potential that Ifosfamide for Injection may cause temporary or permanent infertility [see Use in Specific Populations (8.3)].

Skin and Subcutaneous Tissue Disorders

- Advise patients on the risk of alopecia, wound healing, and other serious skin and subcutaneous tissue disorders [see Warnings and Precautions (5.11), Adverse Reactions (6.2)].

Gastrointestinal Disorders

- Advise patients that the therapy may cause gastrointestinal disorders and alcohol may increase nausea and vomiting [see Adverse Reactions (6.2)].
- Advise patients on the risk of stomatitis and the importance of proper oral hygiene [see Adverse Reactions (6.2)].

Eye Disorders

- Advise patients on the risk of eye disorders such as visual impairment, blurred vision, and eye irritation [see Adverse Reactions (6.2)].

Ear and Labyrinth Disorders

- Advise patients on the risk of ear and labyrinth disorders such as deafness, vertigo, and tinnitus [see Adverse Reactions (6.2)].

Baxter Healthcare Corporation
Deerfield, IL 60015 USA
For Product Inquiry 1-800 ANA DRUG (1-800-262-3784)

Made in Germany

Baxter and Viaflex are trademarks of Baxter International Inc.

PAB is a trademark of B Braun

HA-30-02-466

PACKAGE/LABEL PRINCIPAL DISPLAY PANEL

Container Label

NDC 10019-925-82

Ifosfamide
for Injection

1 g Single Dose Vial
FOR IV USE
Rx only

Baxter logo
Manufactured by
Baxter Healthcare Corporation
Deerfield, IL 60015 USA

460-508-00

LOT/EXP:
JMXXXA
JJJJ - MM

This vial contains 1 g ifosfamide.
Add 20 ml Sterile Water for Injection, USP, or
Sterile Bacteriostatic Water for Injection, USP,
(benzyl alcohol or parabens preserved),
shaking to dissolve, for a reconstituted
concentration of 50 mg per mL.
Store at controlled room temperature 20°C
to 25°C (68°F to 77°F).
Protect from temperatures above 30°C (86°F).
READ ACCOMPANYING PACKAGE INSERT for
detailed indications, dosage, and precautions.

(01) 03310019925820

USA HA-65-01-559 C 129

Carton Label

(01) 00310019925011
(21) XXXXXXXXXXXX
(17) JJMMTT
(10) JMXXA

NDC 10019-925-01

Ifosfamide
for Injection

1 g
Rx only
Single Dose Vial
FOR IV USE

Baxter Logo
Manufactured by
Baxter Healthcare Corporation
Deerfield, IL 60015 USA

HA-80-02-149
USA

This vial contains 1 g ifosfamide.
Add 20 ml Sterile Water for Injection,
USP, or Sterile Bacteriostatic Water
for Injection, USP, (benzyl alcohol or
parabens preserved), shaking to
dissolve, for a reconstituted
concentration of 50 mg per mL.

READ ACCOMPANYING PACKAGE
INSERT for detailed indications,
dosage, and precautions.

Store at controlled room
temperature 20°C to 25°C (68°F to
77°F). Protect from temperatures
above 30°C (86°F).

Constituted solutions should be
refrigerated and used within
24 hours.

460-509-00

C
834

LOT/EXP:

JMXXXA
JJJJ – MM

2617B5071

Bar Code

Container Label

NDC 10019-926-16

Ifosfamide
for Injection

3 g Single Dose Vial
FOR IV USE
Rx only

Baxter logo
Manufactured by
Baxter Healthcare Corporation
Deerfield, IL 60015 USA

460-510-00

LOT/EXP:
JMXXXA
JJJJ - MM

This vial contains 3 g ifosfamIde.

Add 60 ml Sterile Water for Injection, USP, or
Sterile Bacteriostatic Water for Injection, USP,
(benzyl alcohol or parabens preserved), shaking
to dissolve, for a reconstituted concentration of
50 mg per mL.

Store at controlled room temperature 20°C to
25°C (68°F to 77°F). Protect from temperatures
above 30°C (86°F).

READ ACCOMPANYING PACKAGE INSERT for
detailed indications, dosage, and precautions.

(01) 03310019926162

USA HA-65-01-562
C 131

Carton Label

(01) 00310019926025
(21) XXXXXXXXXXXX
(17) JJMMTT
(10) JMXXA

NDC 10019-926-02

Ifosfamide
for Injection

3 g/vial

Rx only

Single Dose Vial
FOR IV USE

Baxter Logo
Manufactured by
Baxter Healthcare Corporation
Deerfield, IL 60015 USA

HA-80-02-152
USA

This vial contains 3 g ifosfamide.
Add 60 ml Sterile Water for
Injection, USP, or Sterile Bacteriostatic
Water for Injection, USP,
(benzyl alcohol or parabens
preserved), shaking to dissolve,
for a reconstituted concentration
of 50 mg per mL.

READ ACCOMPANYING PACKAGE
INSERT for detailed indications,
dosage, and precautions.

Store at controlled room temperature
20°C to 25°C (68°F to 77°F).
Protect from temperatures above
30°C (86°F).

Constituted solutions should
be refrigerated and used within
24 hours.

460-511-00

C
836

FOLDING BOX CAN BE RECYCLED SYMBOL

NDC 10019-926-02

Ifosfamide
for Injection

3 g/vial

Rx only

Single Dose Vial
FOR IV USE

Baxter Logo
Manufactured by
Baxter Healthcare Corporation
Deerfield, IL 60015 USA

LOT/EXP:
JMXXXA
JJJJ - MM

2617B5072

Bar Code